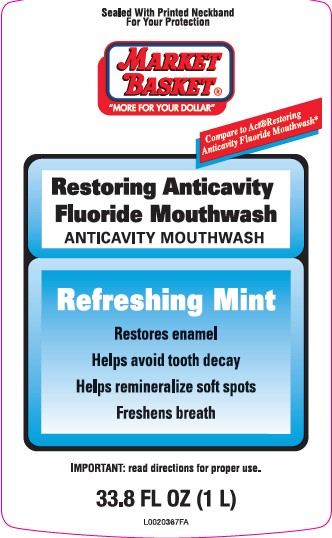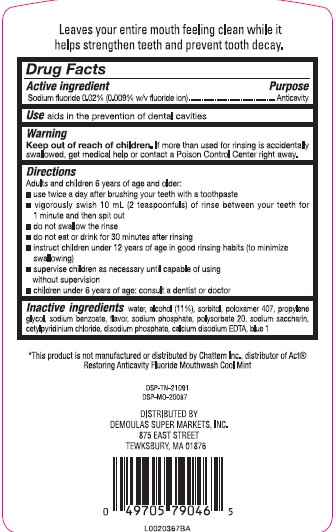 DRUG LABEL: Sodium fluoride
NDC: 53942-581 | Form: MOUTHWASH
Manufacturer: Demoulas Super Markets, Inc
Category: otc | Type: HUMAN OTC DRUG LABEL
Date: 20260203

ACTIVE INGREDIENTS: SODIUM FLUORIDE 0.2 mg/1 mL
INACTIVE INGREDIENTS: SORBITOL; POLOXAMER 407; PROPYLENE GLYCOL; SODIUM BENZOATE; SODIUM PHOSPHATE; POLYSORBATE 20; SACCHARIN SODIUM; CETYLPYRIDINIUM CHLORIDE; SODIUM PHOSPHATE, DIBASIC, ANHYDROUS; EDETATE CALCIUM DISODIUM ANHYDROUS; FD&C BLUE NO. 1; WATER; ALCOHOL

Market Basket 581.000/581AB
Restoring Anticavity Fluoride Mouthwash

Claims

Leaves your entire mouth feeling clean while it helps strengthen teeth and prevent tooth decay.

Active ingredient

Sodium fluoride 0.02% (0.009% w/v fluoride ion)

Purpose

Anticavity

Use

Aids in the prevention of dental cavities

Warning

for this product

Keep out of reach of children.

If more than used for rinsing is accidentally swallowed, get medical help or contact a Poison Control Center right away.

Directions

Adults and children 6 years of age and older:

- use twice a day after brushing your teeth with a toothpaste
- vigorously swish 10 mL (2 teaspoonfuls) of rinse between your teeth for 1 minute and then spit out
- do not swallow the rinse
- do not eat or drink for 30 minutes after rinsing
- instruct children under 12 years of age in good rinsing habits (to minimize swallowing)
- supervise children as necessary until capable of using without supervision
- children under 6 years of age: consult a dentist or doctor

Inactive ingredients

water, alcohol (11%), sorbitol, poloxamer 407, propylene glycol, sodium benzoate, flavor, sodium phosphate, polysorbate 20, sodium saccharin, cetylpyridinium chloride, disodium phosphate, calcium disodium EDTA, blue 1

Adverse reaction

*This product is not manufactured or distributed by Chattem Inc., distributor of Act®Restoring Anticavity Mouthwash Cool Mint

DSP-TN-21091

DSP-MO-20087

DISTRIBUTED BY

DEMOULAS SUPER MARKETS, INC.

875 EAST STREET

TEWKSBURY, MA 01876

Principal Panel Display

Sealed With Printed Neckband For Your Protection

MARKET BASKET®

"MORE FOR YOUR DOLLAR"

Compare to Act®Restoring Anticavity Fluoride Mouthwash*

Restoring Anticavity

Fluoride Mouthwash

ANTICAVITY MOUTHWASH

Refreshing Mint

Restores enamel

Helps avoid tooth decay

Helps remineralize soft spots

Freshens breath

IMPORTANT: read directions for proper use.

33.8 FL OZ (1 L)